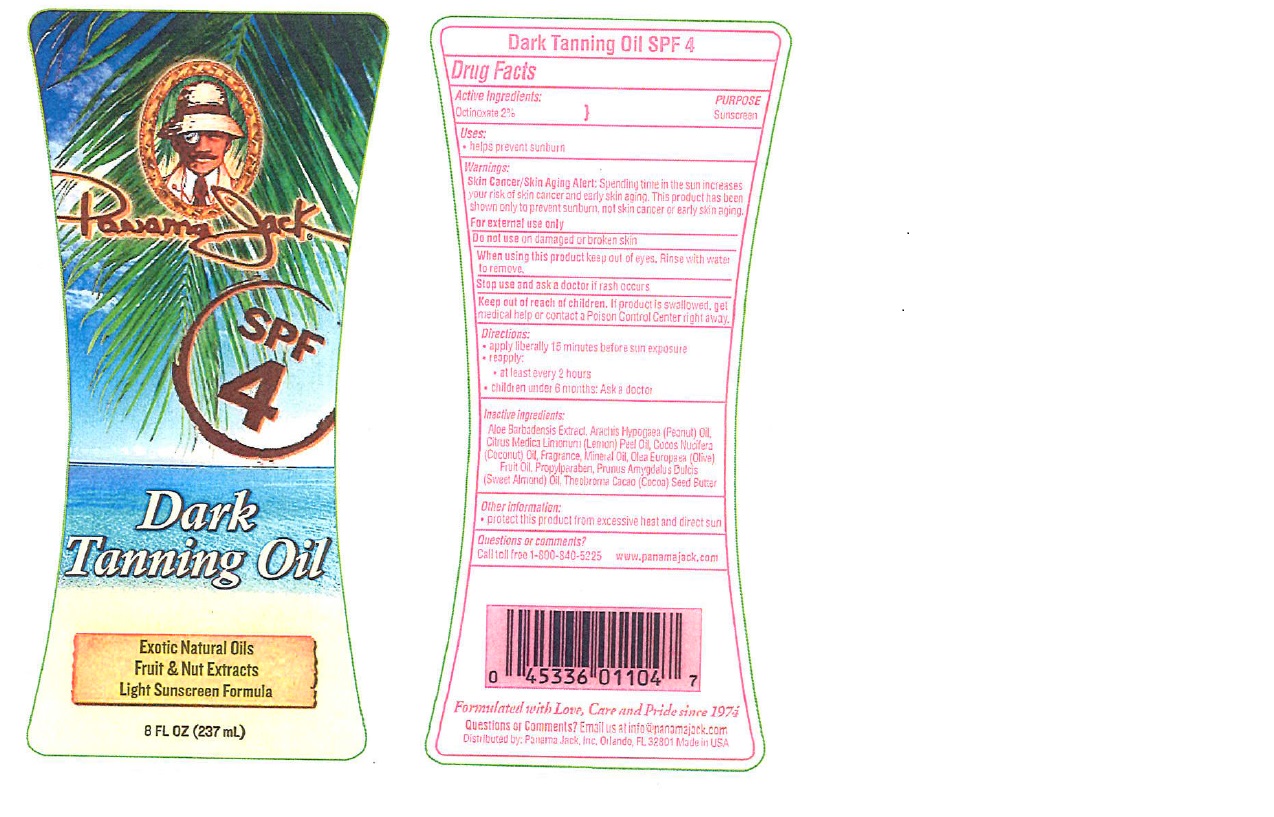 DRUG LABEL: Panama Jack
NDC: 58443-0201 | Form: OIL
Manufacturer: Prime Enterprises Inc.
Category: otc | Type: HUMAN OTC DRUG LABEL
Date: 20200117

ACTIVE INGREDIENTS: OCTINOXATE 2 g/100 g
INACTIVE INGREDIENTS: PEANUT OIL; LEMON OIL; MINERAL OIL; COCONUT OIL; ALOE VERA LEAF; OLIVE OIL; PROPYLPARABEN; ALMOND OIL; COCOA BUTTER

Panama Jack SPF 4 Dark Tanning Oil

Active Ingredients

Octinoxate 2%

Purpose

Sunscreen

Uses

- helps prevent sunburn

Warnings

Skin Cancer/Skin Aging Alert: Spending time in the sun increases your risk of skin cancer and early skin aging. This product has been shown only to prevent sunburn, not skin cancer or early skin aging.

For external use only

Do not use on damaged or broken skin

When using this product keep out of eyes.

Rinse with water to remove.

Stop use and ask a doctor if rash occurs.

Keep out of reach of children. If product is swallowed, get medical help or contact a Poison Control Center right away.

Directions

- apply liberally 15 minutes before sun exposure
- reapply:
- at least every 2 hours
- children under 6 months: Ask a doctor

Inactive Ingredients

Aloe Barbadensis Extract, Arachis Hypogaea (Peanut) Oil, Citrus Medica Limonum (Lemon) Peel Oil, Cocos Nucifera (Coconut) Oil, Fragrance, Mineral Oil, Olea Europaea (Olive) Fruit Oil, Propylparaben, Prunus Amygdalus Dulcis (Sweet Almond) Oil, Theobroma Cacao (Cocoa) Seed Butter

Other Information

- protect this product from excessive heat and direct sun

Questions or comments?

- Call toll free 1-800-840-5225 www.panamajack.com